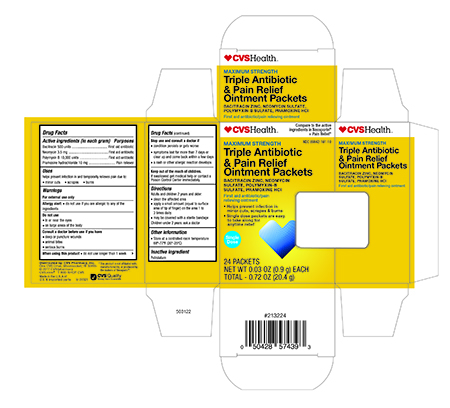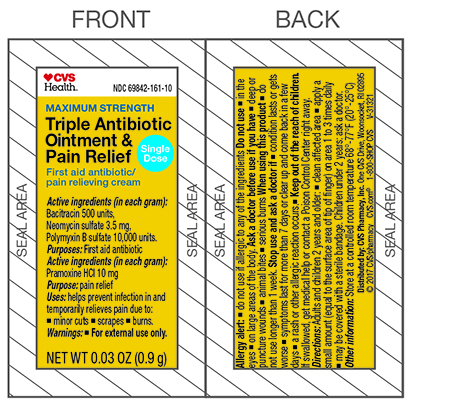 DRUG LABEL: CVS Health  Triple Antibiotic with Pain Relief
NDC: 69842-161 | Form: OINTMENT
Manufacturer: CVS Health
Category: otc | Type: HUMAN OTC DRUG LABEL
Date: 20241111

ACTIVE INGREDIENTS: Bacitracin Zinc 500 [USP'U]/1 g; Polymyxin B Sulfate 10000 [USP'U]/1 g; Neomycin Sulfate 3.5 mg/1 g; PRAMOXINE HYDROCHLORIDE 10 mg/1 g
INACTIVE INGREDIENTS: Petrolatum

Drug Facts

Active ingredients (In each gram)

Bacitracin 500

Neomycin 3.5 mg

Polymyxin B 10,000 units

Pramoxine HCL 10 mg

Purpose

First aid antibiotic

First aid antibiotic

First aid antibiotic

Pain Relief

Uses

helps prevent infection in and temporarily relieves pain due to minor:

- cuts
- scrapes
- burns

Warnings

For external use only

Allergy alert:

- do not use if you are allergic to any of the ingredients

Do not use

- in or near the eyes
- on large areas of the body

Consult a doctor before use if you have

- deep or puncture wounds
- animal bites
- serious burns

When using this product

- do not use longer than 1 week

Stop use and consult a doctor if

- condition persists or gets worse
- symptoms last for more than 7 days or clear up and come back within a few days
- a rash or other allergic reaction develops

KEEP OUT OF REACH OF CHILDREN

Keep out of the reach of children. If swallowed get medical help or contact a Poison Control Center immediately.

Directions

- clean the affected area
- apply a small amount (equal to surface area of tip of finger) on the area 1 to 3 times daily.
- may be covered with a sterile bandage

Other information

- Store at a controlled room temperature 68º-77ºF (20º-25ºC)

Inactive ingredient

Petrolatum

Principal Display Panel – Packet Label

CVS Health NDC 69842-161-10

Triple Antibiotic Ointment & Pain Relief Bacitracin Zinc • Neomycin Sulfate • Polymyxin-B Sulfate• Pramoxine HCL
First Aid Antibiotic/Pain relieving Ointment

NET WT. 0.03 oz. (0.9g)

Principal Display Panel – Carton Label

CVS Health NDC 69842-161-10

Triple Antibiotic & Pain Relief Ointment

Bacitracin Zinc • Neomycin Sulfate • Polymyxin-B Sulfate•Pramoxine HCL
First Aid Antibiotic /Pain relieving Ointment

24 packets

NET WT. 0.72 oz. (20.4g)
First Aid Treatment for Minor Cuts, Scrapes and Burns